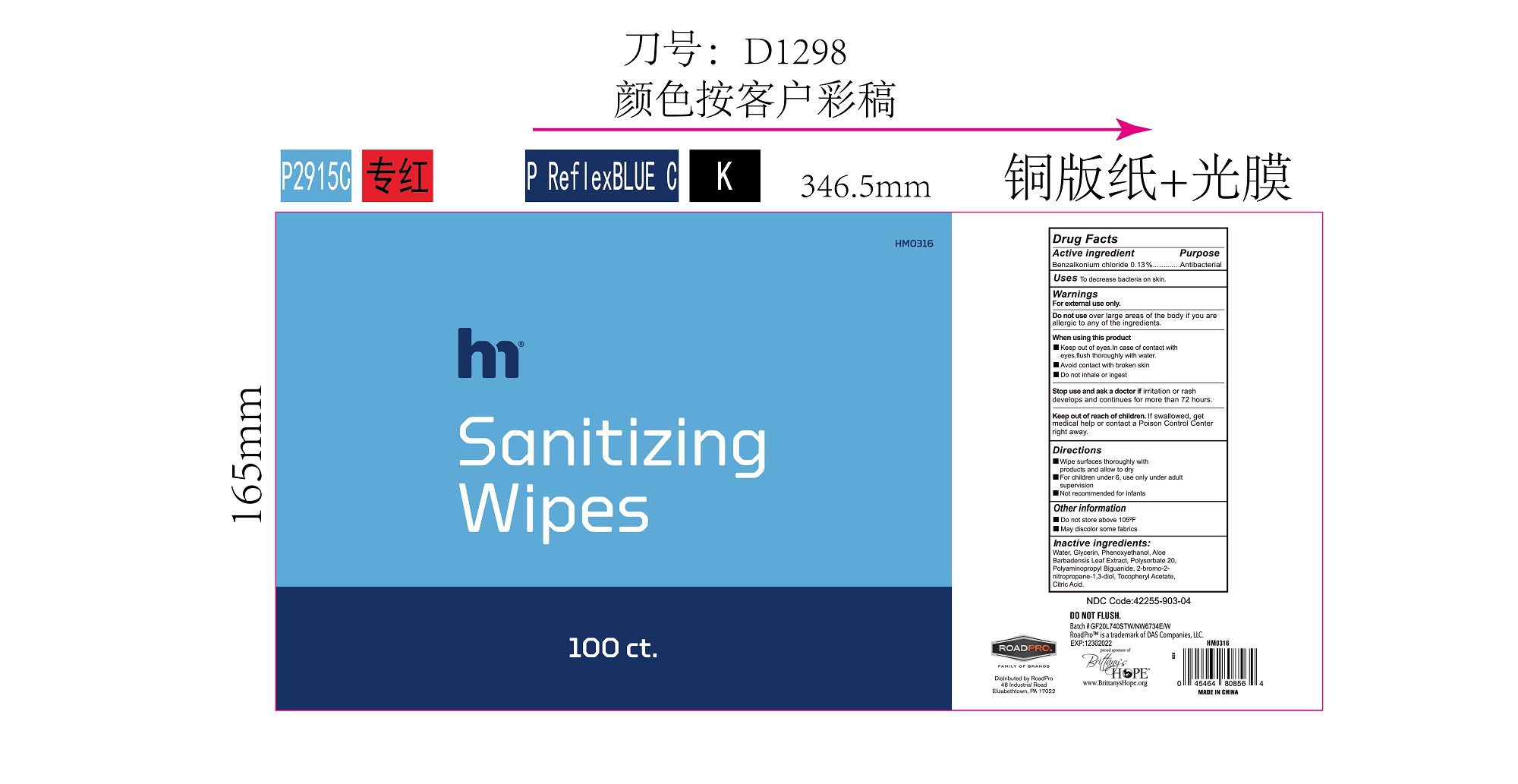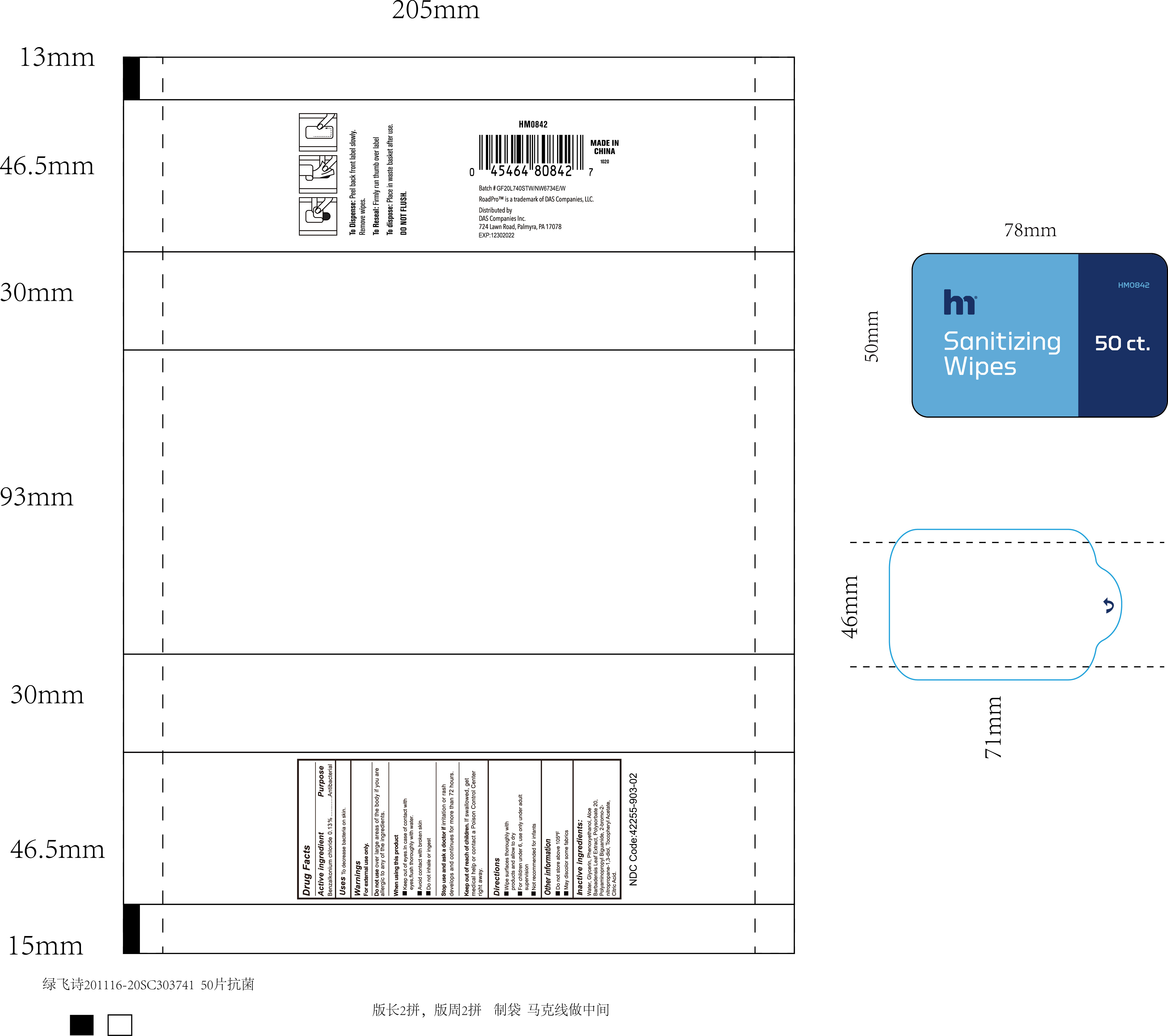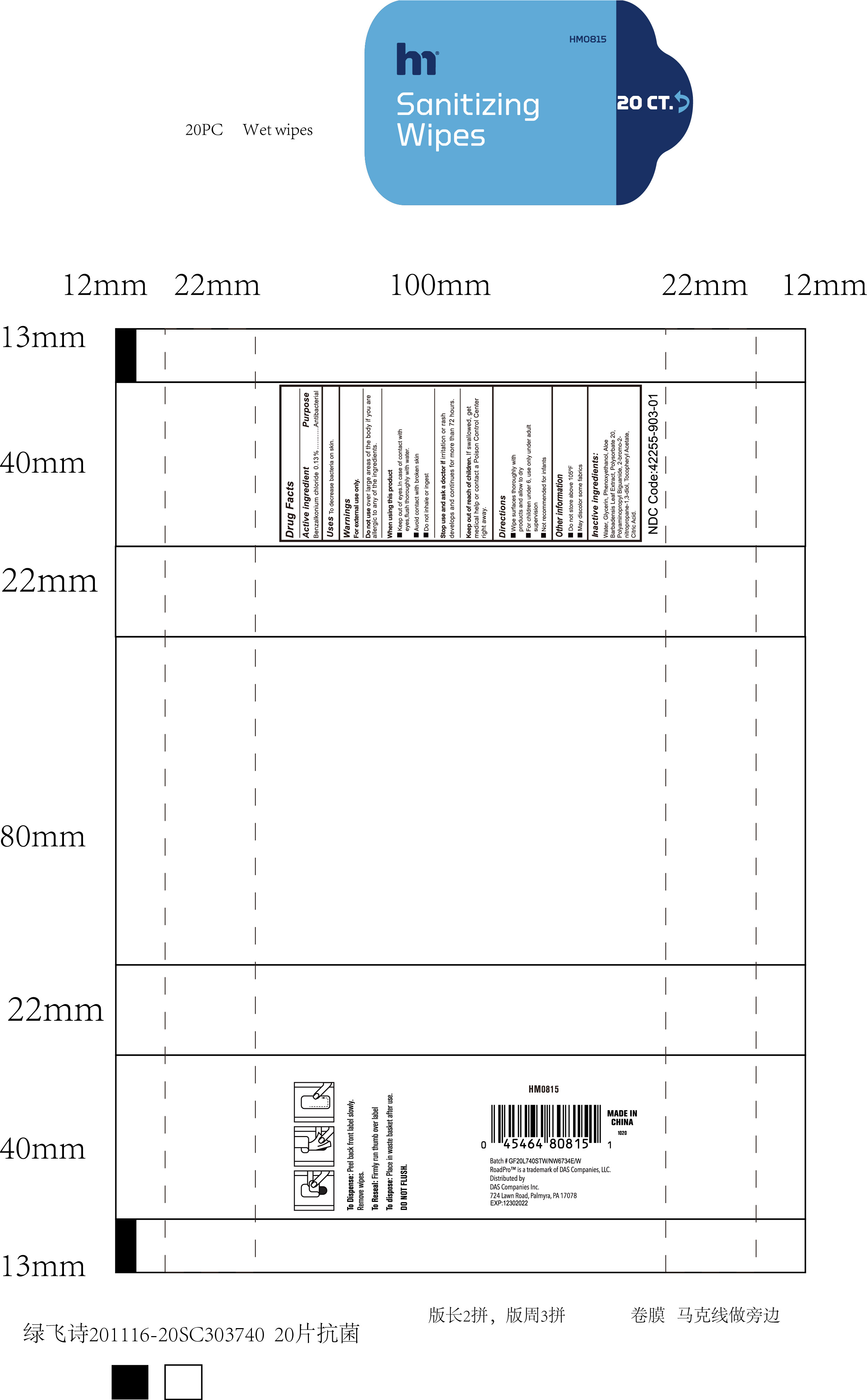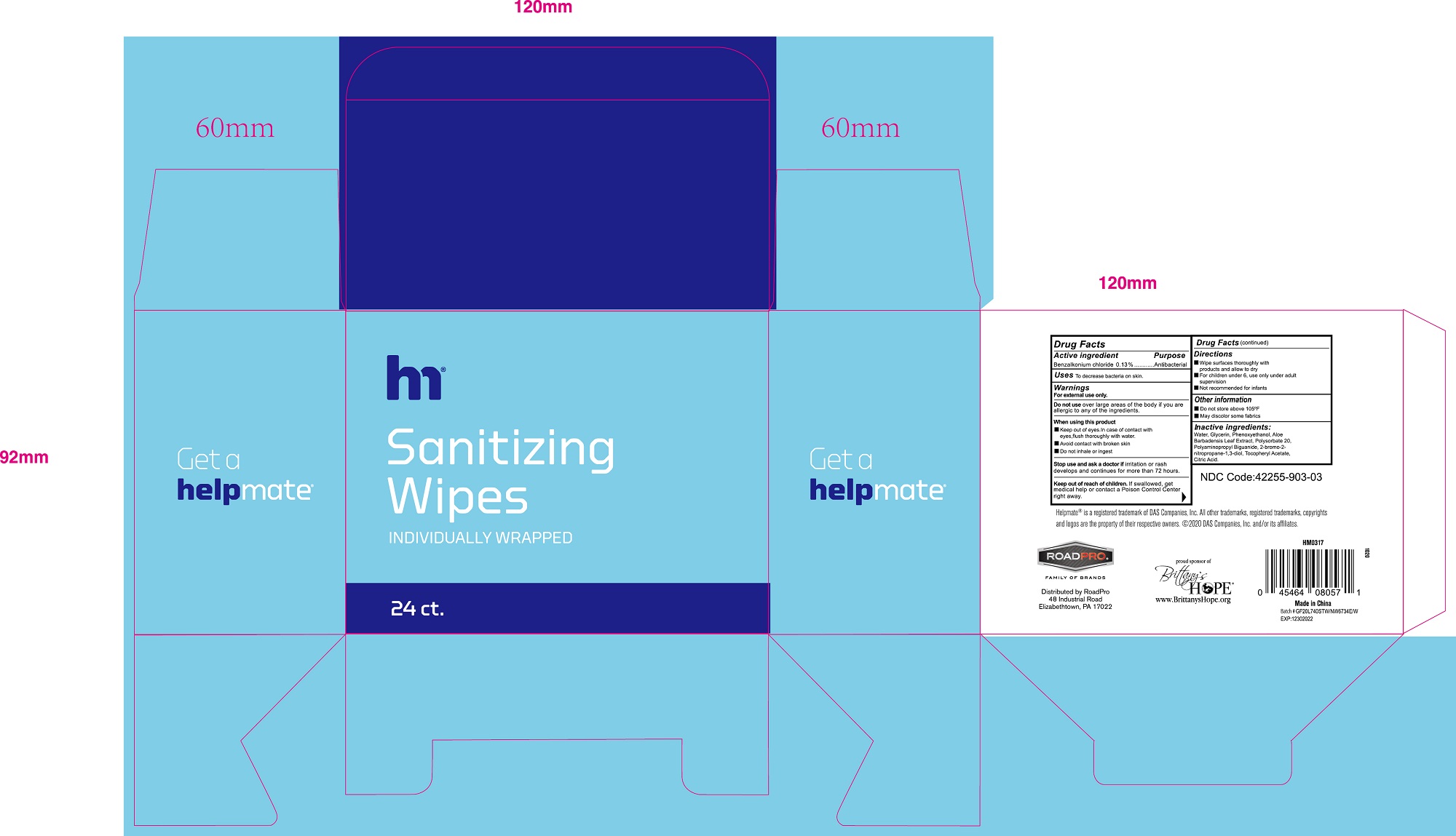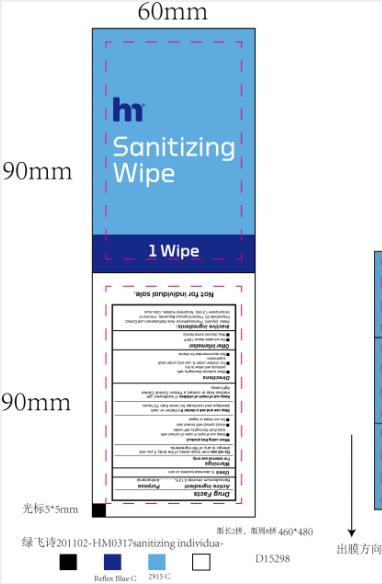 DRUG LABEL: helpmate sanitizing wipes
NDC: 42255-903 | Form: CLOTH
Manufacturer: ZHEJIANG GREENFACE HOUSEWARES CO., LTD.
Category: otc | Type: HUMAN OTC DRUG LABEL
Date: 20201204

ACTIVE INGREDIENTS: BENZALKONIUM CHLORIDE 0.13 g/100 g
INACTIVE INGREDIENTS: PHENOXYETHANOL; GLYCERIN; BRONOPOL; ALOE VERA LEAF; ALPHA-TOCOPHEROL ACETATE; WATER; POLYAMINOPROPYL BIGUANIDE; CITRIC ACID MONOHYDRATE; POLYSORBATE 20

42255-903 helpmate sanitizing wipes 0.13% benzalkonium chloride

Active ingredient

Benzalkonium chloride 0.13%

Purpose

Antibacterial

Use

decreases bacteria on skin

Warnings

For external use only.
Do not use over large areas of the body if you are
allergic to any of the ingredients.
When using this product
Keep out of eyes.In case of contact with
eyes,flush thoroughly with water.
Avoid contact with broken skin
Do not inhale or ingest
Stop use and ask a doctor if irritation or rash
develops and continues for more than 72 hours.

Keep out of reach of children

if swallowed

get medical help or contact a Poison Control Center right away.

Directions

wipe surfaces thoroughly with products and allow to dry
For children under 6, use only under adult supervision
Not recommended for infants

INACTIVE INGREDIENT

Water,Glycerin, Phenoxyethanol,Aloe
Barbadensis Leaf Extract, Polysorbate 20,Polyaminopropyl Biguanide, 2-bromo-2-
nitropropane-1,3-diol,Tocopheryl Acetate,Citric Acid.